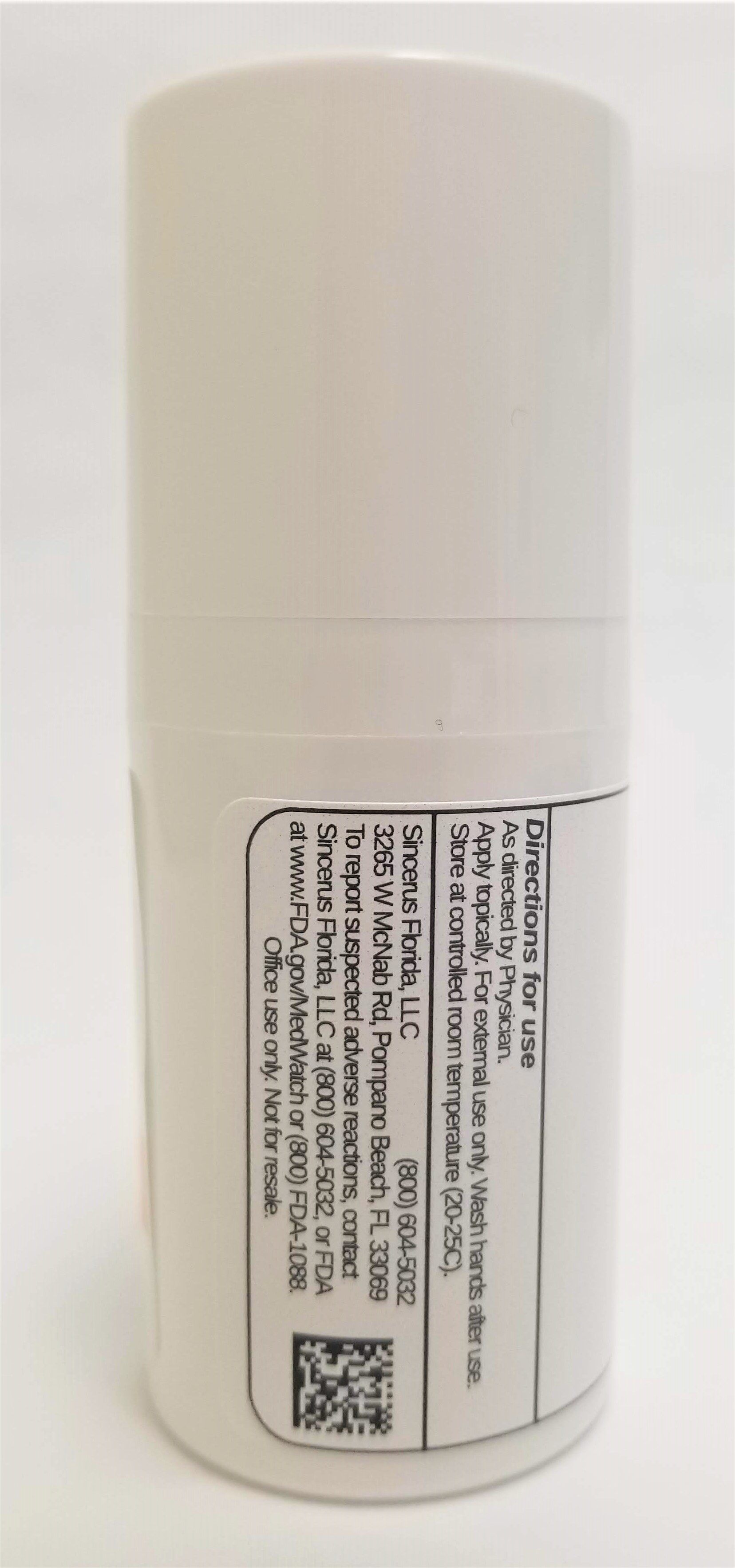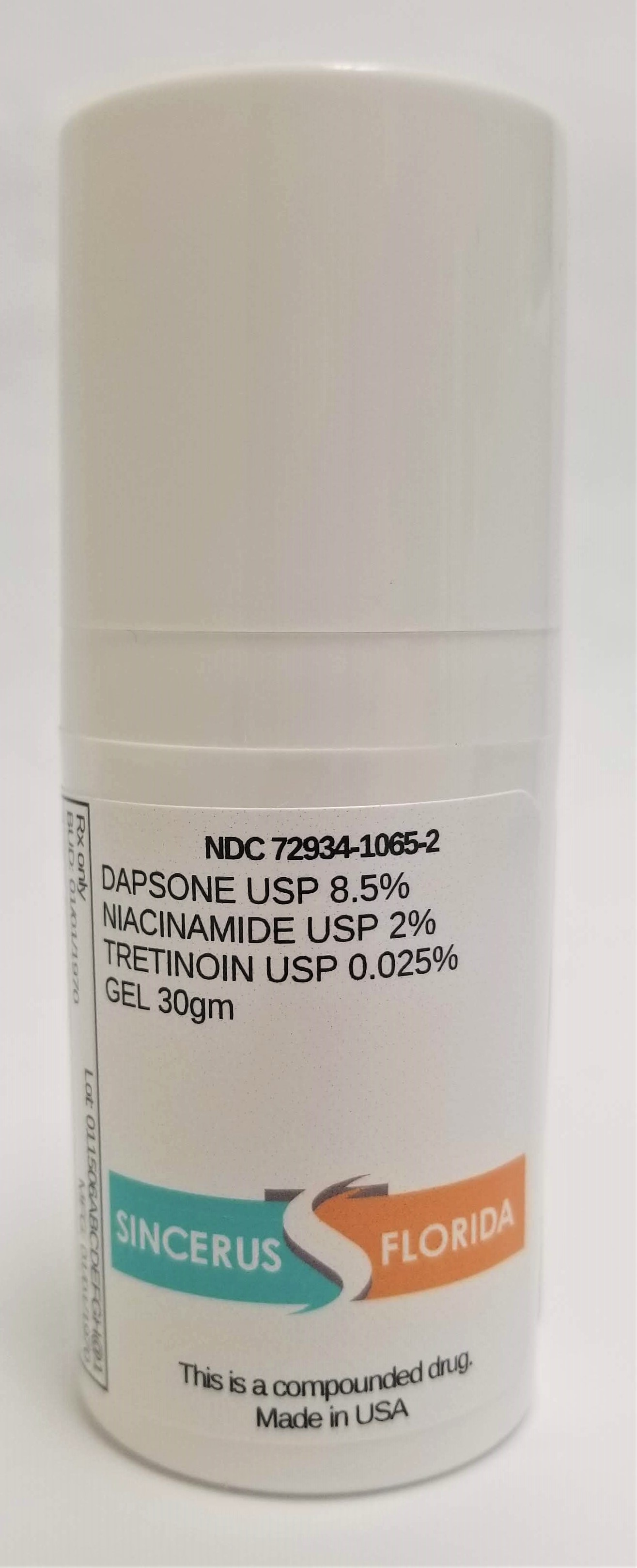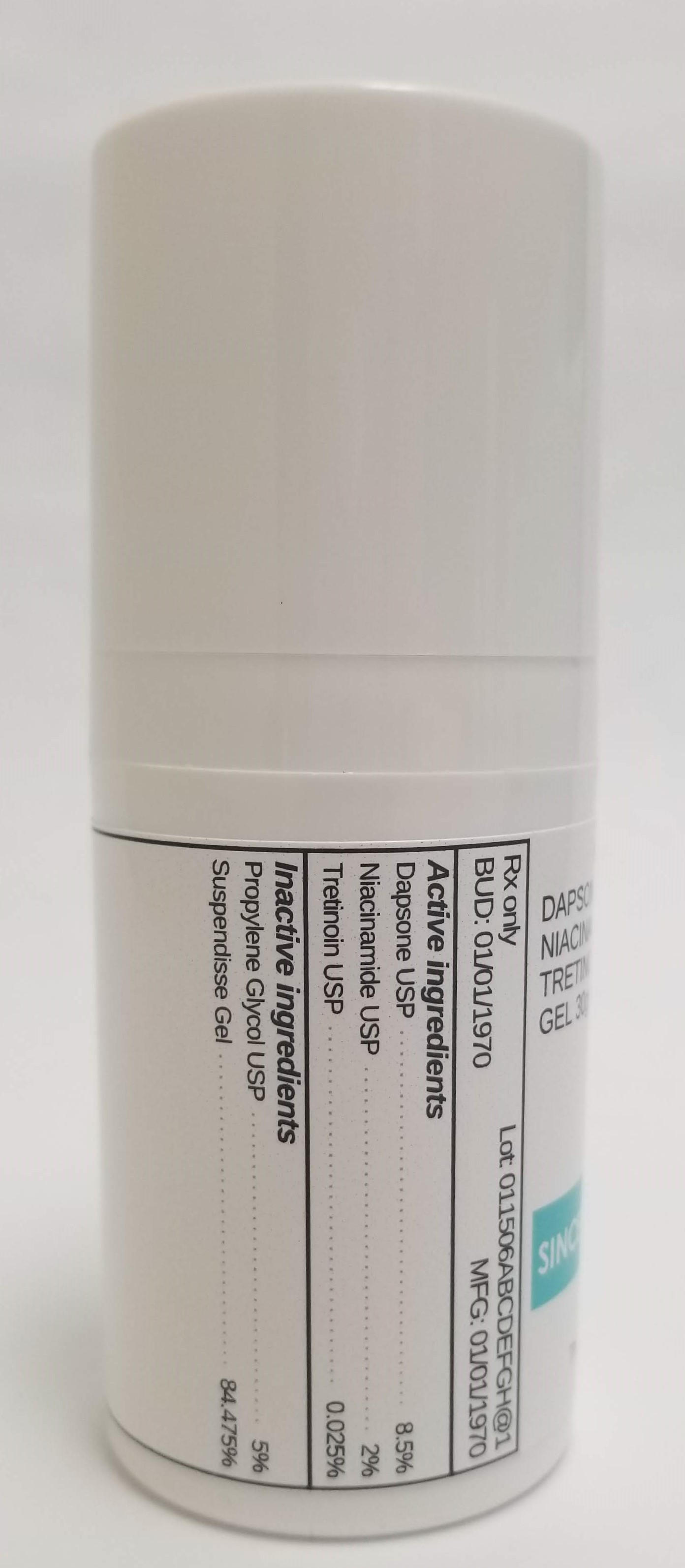 DRUG LABEL: DAPSONE 8.5% / NIACINAMIDE 2% / TRETINOIN 0.025%
NDC: 72934-1065 | Form: GEL
Manufacturer: Sincerus Florida LLC
Category: prescription | Type: HUMAN PRESCRIPTION DRUG LABEL
Date: 20190502

ACTIVE INGREDIENTS: DAPSONE 8.5 g/100 g; TRETINOIN 0.025 g/100 g; NIACINAMIDE 2 g/100 g

DAPSONE 8.5% / NIACINAMIDE 2% / TRETINOIN 0.025%